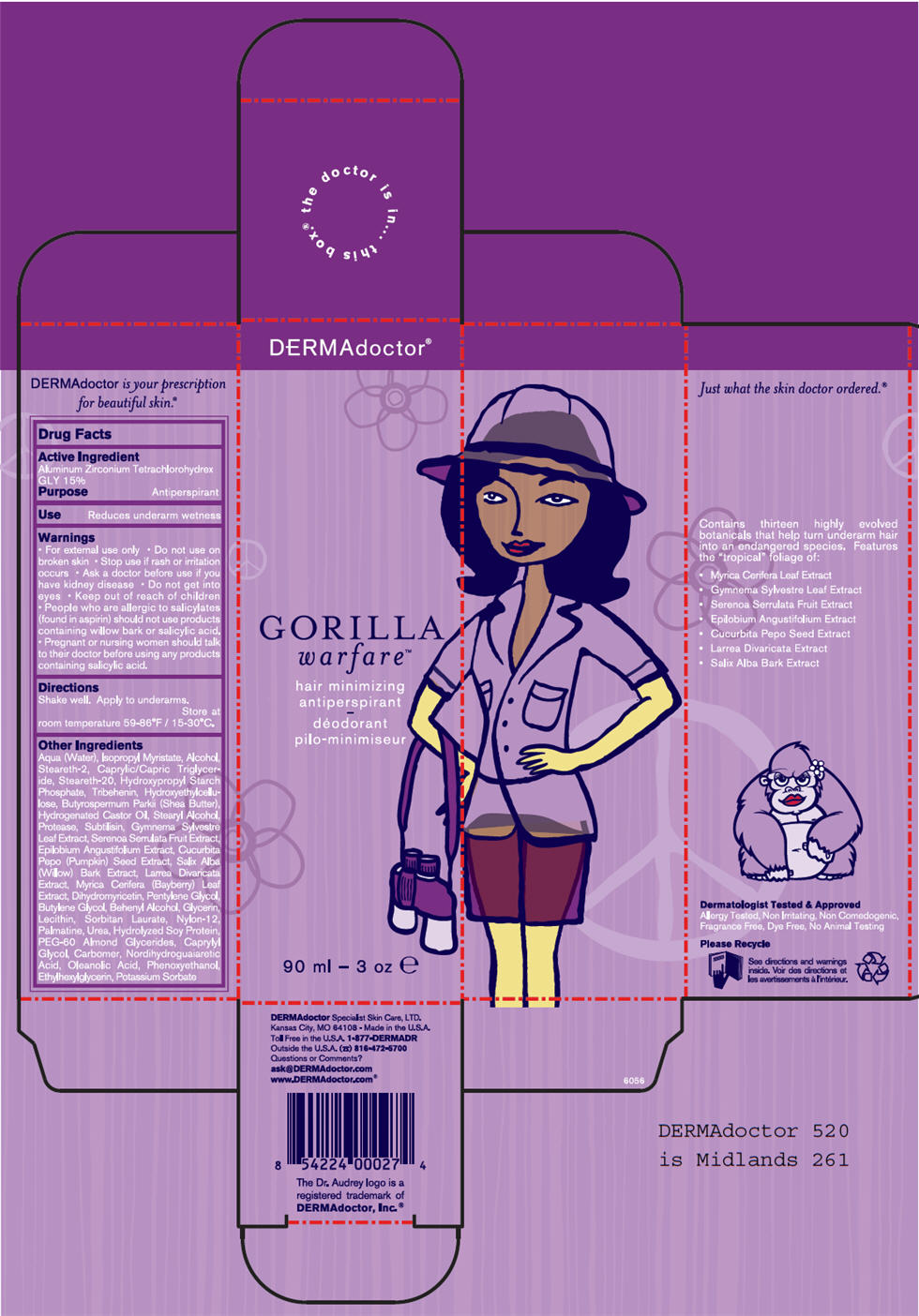 DRUG LABEL: GORILLA WARFARE
NDC: 65113-2428 | Form: LOTION
Manufacturer: G.S. COSMECEUTICAL USA, INC.
Category: otc | Type: HUMAN OTC DRUG LABEL
Date: 20100924

ACTIVE INGREDIENTS: ALUMINUM ZIRCONIUM TETRACHLOROHYDREX GLY 15 mL/100 mL
INACTIVE INGREDIENTS: Water; Isopropyl Myristate; Alcohol; Steareth-2; MEDIUM-CHAIN TRIGLYCERIDES; Steareth-20; Tribehenin; Shea Butter; Hydrogenated Castor Oil; Stearyl Alcohol; Aspergillus Flavus Var. Oryzae Protease; Saw Palmetto; Pumpkin Seed; Salix Alba Bark; Larrea Tridentata Top; Pentylene Glycol; Butylene Glycol; Docosanol; Glycerin; Sorbitan Monolaurate; Palmatine; Urea; PEG-60 Almond Glycerides; Caprylyl Glycol; Masoprocol; Oleanolic Acid; Phenoxyethanol; Ethylhexylglycerin; Potassium Sorbate

GORILLA
warfare™

Drug Facts

Active Ingredient

Aluminum Zirconium Tetrachlorohydrex GLY 15%

Purpose

Antiperspirant

Use

Reduces underarm wetness

Warnings

- For external use only

- Do not use on broken skin

- Stop use if rash or irritation occurs

- Ask a doctor before use if you have kidney disease

WHEN USING

- Do not get into eyes

- Keep out of reach of children

DO NOT USE

- People who are allergic to salicylates (found in aspirin) should not use products containing willow bark or salicylic acid.

PREGNANCY OR BREAST FEEDING

- Pregnant or nursing women should talk to their doctor before using any products containing salicylic acid.

Directions

Shake well. Apply to underarms.

STORAGE AND HANDLING

Store at room temperature 59-86°F / 15-30°C.

Other Ingredients

Aqua (Water), Isopropyl Myristate, Alcohol, Steareth-2, Caprylic/Capric Triglyceride, Steareth-20, Hydroxypropyl Starch Phosphate, Tribehenin, Hydroxyethylcellulose, Butyrospermum Parkii (Shea Butter), Hydrogenated Castor Oil, Stearyl Alcohol, Protease, Subtilisin, Gymnema Sylvestre Leaf Extract, Serenoa Serrulata Fruit Extract, Epilobium Angustifolium Extract, Cucurbita Pepo (Pumpkin) Seed Extract, Salix Alba (Willow) Bark Extract, Larrea Divaricata Extract, Dihydromyricetin, Pentylene Glycol, Butylene Glycol, Behenyl Alcohol, Glycerin, Lecithin, Sorbitan Laurate, Nylon-12, Palmatine, Urea, Hydrolyzed Soy Protein, PEG-60 Almond Glycerides, Caprylyl Glycol, Carbomer, Nordihydroguaiaretic Acid, Oleanolic Acid, Phenoxyethanol, Ethylhexylglycerin, Potassium Sorbate

Questions or Comments?

ask@DERMAdoctor.com

www.DERMAdoctor.com®

PRINCIPAL DISPLAY PANEL - 90 mL Carton

DERMAdoctor®

GORILLA
warfare™

hair minimizing
antiperspirant

90 ml - 3 oz e